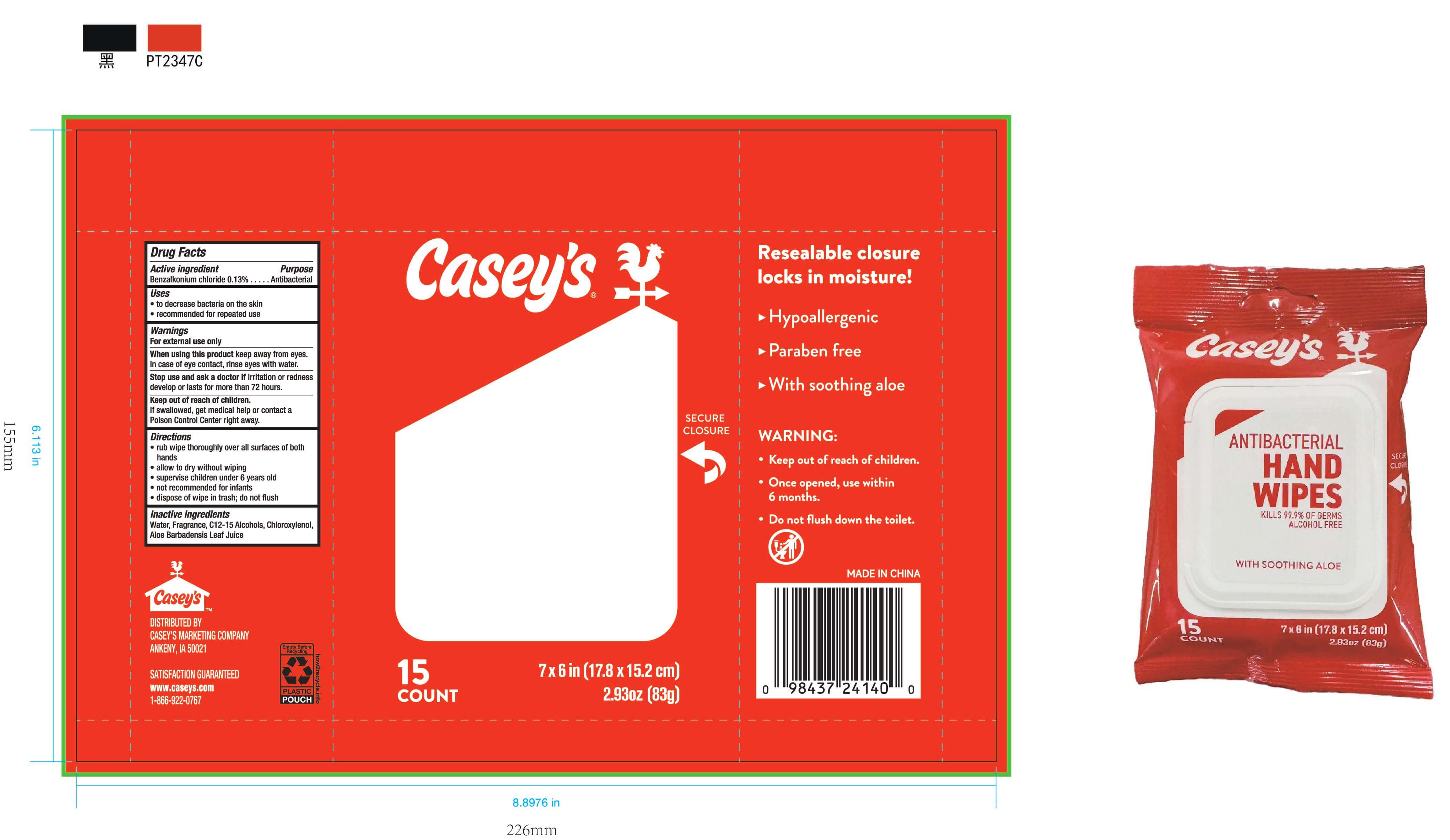 DRUG LABEL: Caseys
NDC: 85844-001 | Form: SOLUTION
Manufacturer: Zhejiang Bright Care Co., Ltd.
Category: otc | Type: HUMAN OTC DRUG LABEL
Date: 20250830

ACTIVE INGREDIENTS: BENZALKONIUM CHLORIDE 0.13 g/100 g
INACTIVE INGREDIENTS: WATER; CHLOROXYLENOL; C12-15 ALCOHOLS; ALOE BARBADENSIS LEAF JUICE

85844-001 Casey's

Active ingredient

BENZALKONIUM CHLORIDE 0.13%

Purpose

Antibacterial

Uses

- To decrease bacteria on the skin
- Recommended for repeated use

Warnings

For external use only.

When using this product, keep away from eyes. In case of eye contact, rinse eyes with water

Stop use and ask a doctor if irritation or redness develops or lasts for more than 72 hours

Keep out of reach of children. If swallowed, get medical help or contact a Poison Control Center right away.

Directions:

- rub wipe thoroughly over all surfaces of both hands
- allow to dry without wiping
- superwise children under 6 years old
- not recommended for infants
- dispose of wipe in trash, do not flush

Inactive ingredients

Water, Fragrance, C12-15 Alcohols, Chloroxylenol, Aloe Barbadensis Leaf Juice